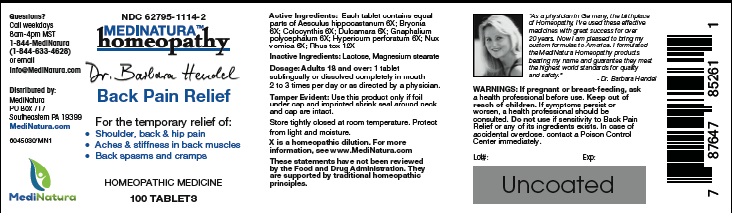 DRUG LABEL: Dr. Hendel Back Pain Relief
NDC: 62795-1114 | Form: TABLET
Manufacturer: MediNatura Inc
Category: homeopathic | Type: HUMAN OTC DRUG LABEL
Date: 20220818

ACTIVE INGREDIENTS: HORSE CHESTNUT 6 [hp_X]/1 1; BRYONIA ALBA ROOT 6 [hp_X]/1 1; CITRULLUS COLOCYNTHIS FRUIT PULP 6 [hp_X]/1 1; SOLANUM DULCAMARA TOP 6 [hp_X]/1 1; PSEUDOGNAPHALIUM OBTUSIFOLIUM 6 [hp_X]/1 1; HYPERICUM PERFORATUM 6 [hp_X]/1 1; STRYCHNOS NUX-VOMICA SEED 6 [hp_X]/1 1; TOXICODENDRON PUBESCENS LEAF 12 [hp_X]/1 1
INACTIVE INGREDIENTS: LACTOSE MONOHYDRATE; MAGNESIUM STEARATE

Dr. Hendel Back Pain Relief

WARNINGS

If pregnant or breast-feeding, ask a health professional before use. Keep out of reach of children. If symptoms persist or worsen, a health professional should be consulted. Do not use if sensitivity to Hendel Back Pain Relief or any of its ingredients exists. In case of accidental overdose, contact a Poison Control Center immediately.

KEEP OUT OF REACH OF CHILDREN

INDICATIONS

Back Pain Relief

ACTIVE INGREDIENT

Each tablet containsequal parts of: Aesculus hippocastanum 6X; Bryonia 6X; Colocynthis 6X; Dulcamara 6X; Gnaphalium polycephalum 6X; Hypericum perforatum 6X; Nux vomica 6X; Rhus tox 12X

INACTIVE INGREDIENT

Lactose, Magnesium stearate

DIRECTIONS

Dosage: Adults 18 and over: 1 tablet sublingually or dissolved completely in mouth 2 to 3 times per day or as directed by a physician.

USES

For the temporary relief of:

- Shoulder, back & hip pain
- Aches & stiffness in back muscles
- Back spasms and cramps

PACKAGE LABEL

Add image transcription here...